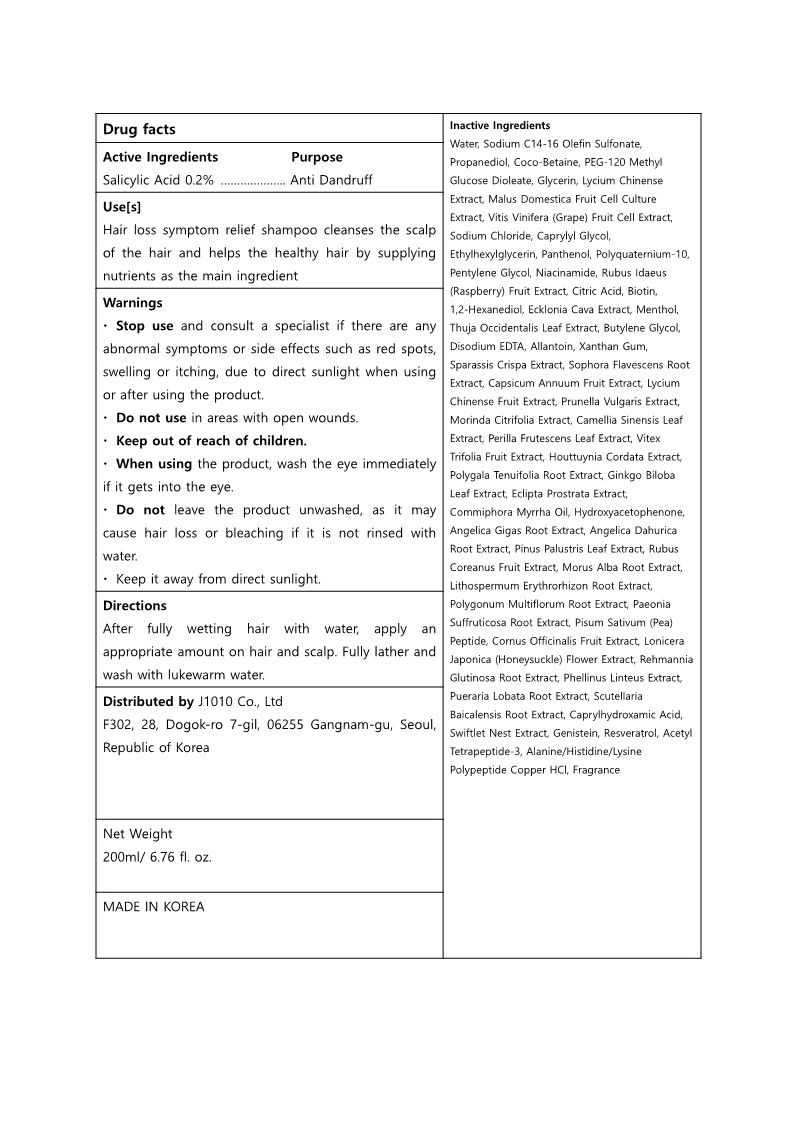 DRUG LABEL: Maetria Miracle Recipe PremiumShampoo
NDC: 82934-401 | Form: SHAMPOO
Manufacturer: J 1010 Co., Ltd.
Category: otc | Type: HUMAN OTC DRUG LABEL
Date: 20221013

ACTIVE INGREDIENTS: SALICYLIC ACID 1 g/100 mL
INACTIVE INGREDIENTS: PEG-120 METHYL GLUCOSE DIOLEATE; LYCIUM CHINENSE FRUIT; PRUNELLA VULGARIS; MORINDA CITRIFOLIA LEAF; ANGELICA DAHURICA ROOT; LITHOSPERMUM ERYTHRORHIZON ROOT; PAEONIA X SUFFRUTICOSA ROOT; CORNUS OFFICINALIS FRUIT; PEA; ACENEURAMIC ACID; WINE GRAPE; SODIUM C14-16 OLEFIN SULFONATE; ETHYLHEXYLGLYCERIN; PANTHENOL; NIACINAMIDE; PUERARIA MONTANA VAR. LOBATA ROOT; ALANINE; WATER; PHELLINUS LINTEUS WHOLE; HOUTTUYNIA CORDATA FLOWERING TOP; ECLIPTA PROSTRATA LEAF; SODIUM CHLORIDE; GREEN TEA LEAF; GINKGO; MYRRH OIL; HYDROXYACETOPHENONE; RASPBERRY; CITRIC ACID MONOHYDRATE; BIOTIN; 1,2-HEXANEDIOL; ECKLONIA CAVA; MENTHOL; THUJA OCCIDENTALIS LEAF; SPARASSIS CRISPA FRUITING BODY; PERILLA FRUTESCENS LEAF; VITEX TRIFOLIA FRUIT; POLYGALA TENUIFOLIA ROOT; ANGELICA GIGAS ROOT; SODIUM SULFATE; TETRADECENE; HEXADECENE (MIXED ISOMERS); CAPRYLYL GLYCOL; COCO-BETAINE; GLYCERIN; PROPANEDIOL; POLYQUATERNIUM-10 (1000 MPA.S AT 2%); PENTYLENE GLYCOL; BUTYLENE GLYCOL; ALLANTOIN; PINUS PALUSTRIS LEAF; RUBUS COREANUS FRUIT; MORUS ALBA ROOT; REYNOUTRIA MULTIFLORA ROOT; LONICERA JAPONICA FLOWER; REHMANNIA GLUTINOSA ROOT; RESVERATROL; FRAGRANCE FLORAL ORC0902236; ACETYL TETRAPEPTIDE-3; SCUTELLARIA BAICALENSIS ROOT; CAPRYLHYDROXAMIC ACID; EDETATE DISODIUM ANHYDROUS; XANTHAN GUM; SOPHORA FLAVESCENS ROOT; PAPRIKA; GENISTEIN

82934-401 Maetria Miracle Recipe Premium Shampoo

Active ingredients

Salicylic Acid 0.2%

Purpose

Salicylic Acid 0.2% ……………….. Anti Dandruff

Uses

Hair loss symptom relief shampoo cleanses the scalp of the hair and helps the healthy hair by supplying nutrients as the main ingredient

Warnings

· Stop use and consult a specialist if there are any abnormal symptoms or side effects such as red spots, swelling or itching, due to direct sunlight when using or after using the product.
· Do not use in areas with open wounds. · Keep out of reach of children.
· When using the product, wash the eye immediately if it gets into the eye.
· Do not leave the product unwashed, as it may cause hair loss or bleaching if it is not rinsed with water.
· Keep it away from direct sunlight.

Warnings

When using the product, wash the eye immediately if it gets into the eye.

Warnings

Stop use and consult a specialist if there are any abnormal symptoms or side effects such as red spots, swelling or itching, due to direct sunlight when using or after using the product.

Warnings

Keep out of reach of children.

Warnings

Do not use in areas with open wounds.

Directions

After fully wetting hair with water, apply an appropriate amount on hair and scalp. Fully lather and wash with lukewarm water.

Inactive ingredients

Water, Sodium C14-16 Olefin Sulfonate, Propanediol, Coco-Betaine, PEG-120 Methyl Glucose Dioleate, Glycerin, Lycium Chinense Extract, Malus Domestica Fruit Cell Culture Extract, Vitis Vinifera (Grape) Fruit Cell Extract, Sodium Chloride, Caprylyl Glycol, Ethylhexylglycerin, Panthenol, Polyquaternium-10, Pentylene Glycol, Niacinamide, Rubus Idaeus (Raspberry) Fruit Extract, Citric Acid, Biotin,
1,2-Hexanediol, Ecklonia Cava Extract, Menthol, Thuja Occidentalis Leaf Extract, Butylene Glycol, Disodium EDTA, Allantoin, Xanthan Gum, Sparassis Crispa Extract, Sophora Flavescens Root Extract, Capsicum Annuum Fruit Extract, Lycium Chinense Fruit Extract, Prunella Vulgaris Extract, Morinda Citrifolia Extract, Camellia Sinensis Leaf Extract, Perilla Frutescens Leaf Extract, Vitex Trifolia Fruit Extract, Houttuynia Cordata Extract, Polygala Tenuifolia Root Extract, Ginkgo Biloba Leaf Extract, Eclipta Prostrata Extract, Commiphora Myrrha Oil, Hydroxyacetophenone, Angelica Gigas Root Extract, Angelica Dahurica Root Extract, Pinus Palustris Leaf Extract, Rubus Coreanus Fruit Extract, Morus Alba Root Extract, Lithospermum Erythrorhizon Root Extract, Polygonum Multiflorum Root Extract, Paeonia Suffruticosa Root Extract, Pisum Sativum (Pea) Peptide, Cornus Officinalis Fruit Extract, Lonicera Japonica (Honeysuckle) Flower Extract, Rehmannia Glutinosa Root Extract, Phellinus Linteus Extract, Pueraria Lobata Root Extract, Scutellaria Baicalensis Root Extract, Caprylhydroxamic Acid, Swiftlet Nest Extract, Genistein, Resveratrol, Acetyl Tetrapeptide-3, Alanine/Histidine/Lysine Polypeptide Copper HCl, Fragrance